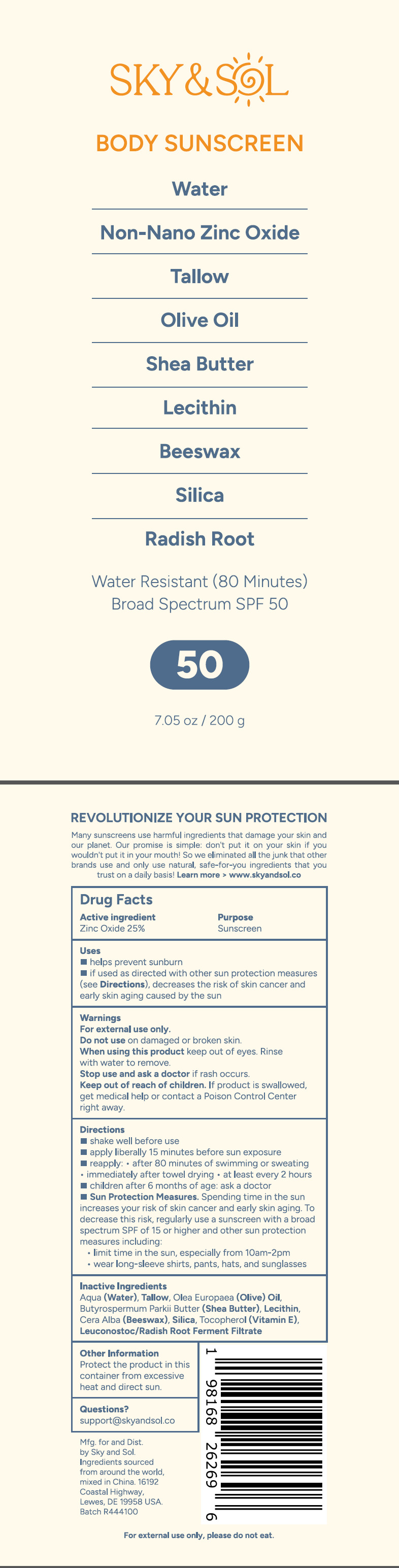 DRUG LABEL: Sky and Sol Body Sunscreen SPF50
NDC: 83447-011 | Form: CREAM
Manufacturer: Guangzhou Fantesy Biotechnology Co.,Ltd
Category: otc | Type: HUMAN OTC DRUG LABEL
Date: 20250211

ACTIVE INGREDIENTS: ZINC OXIDE 25 g/100 g
INACTIVE INGREDIENTS: AQUA; OLEA EUROPAEA (OLIVE) FRUIT OIL; TALLOW; BUTYROSPERMUM PARKII (SHEA) BUTTER; LECITHIN, SOYBEAN; CYPROHEPTADINE; SILICA; TOCOPHEROL; LEUCONOSTOC/RADISH ROOT FERMENT FILTRATE

83447-011
Sky and Sol Body Sunscreen SPF50

Active ingredients

Zinc Oxide 25%

Purpose

Sunscreen

Uses

■ Helps prevent sunburn

■ if used as directed with other sun protection measures (see Directions), decreases the risk of skin cancer and
early skin aging caused by the sun

Warnings

For external use only.

Do not use on damaged or broken skin.

When using this product, keep out of eyes. Rinse with water to remove.

Stop use

Stop use and ask a doctor if rash occurs.

Keep out of reach of children . If product is swallowed . get medical help or contact a Poison Control Center right away.

Directions

1.shake well before use
2.apply liberally 15 minutes before sun exposure
3.reapply:●after 80 minutes of swimming or sweating ●immediately after towel drying●at least every 2 hours
4.children after 6 months of age: ask a doctor
5.Sun Protection Measures. Spending time in the sun increases your risk of skin cancer and early skin aging. To
decrease this risk, regularly use a sunscreen with a broad spectrum SPF of 15 or higher and other sun protection
measures including:
●limit time in the sun, especially from 10am-2pm
●wear long-sleeve shirts, pants, hats, and sunglasses

Other information

Protect the product in this container from excessive heat and direct sun.

Inactive ingredients

Aqua (Water), Tllow, Olea Europaea (Olive) Oil, Butyrospermum Parki Butter (Shea Butter), Lecithin,
Cera Alba (Beeswax), Silica, Tocopherol (Vitamin E), Leuconostoc/Radish Root Ferment Filtrate